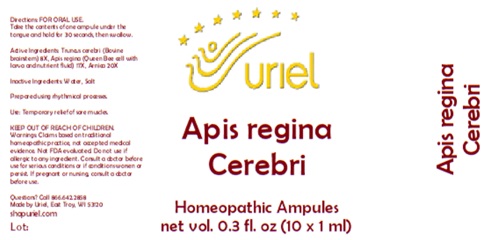 DRUG LABEL: Apis Regina Cerebri
NDC: 48951-1061 | Form: LIQUID
Manufacturer: Uriel Pharmacy Inc.
Category: homeopathic | Type: HUMAN OTC DRUG LABEL
Date: 20250916

ACTIVE INGREDIENTS: BOS TAURUS BRAINSTEM 8 [hp_X]/1 mL; ROYAL JELLY 17 [hp_X]/1 mL; ASTRAGALUS PROPINQUUS ROOT 20 [hp_X]/1 mL
INACTIVE INGREDIENTS: WATER; SODIUM CHLORIDE

Apis Regina Cerebri

INDICATIONS AND USAGE

Directions: FOR ORAL USE.

DOSAGE AND ADMINISTRATION

Take the contents of one ampule under the tongue and hold for 30 seconds, then swallow.

ACTIVE INGREDIENT

Active Ingredients: Truncus cerebri (Bovine brainstem) 8X, Apis regina (Queen Bee cell with larva and nutrient fluid) 17X, Arnica 20X

Inactive Ingredients: Water, Salt

Prepared using rhythmical processes.

PURPOSE

Use: Temporary relief of sore muscles.

KEEP OUT OF REACH OF CHILDREN.

WARNINGS

Warnings: Claims based on traditional homeopathic practice, not accepted medical evidence. Not FDA evaluated. Do not use if allergic to any ingredient. Consult a doctor before use for serious conditions or if conditions worsen or persist. If pregnant or nursing, consult a doctor before use.

Questions? Call 866.642.2858
Made by Uriel, East Troy, WI 53120
shopuriel.com

Lot: